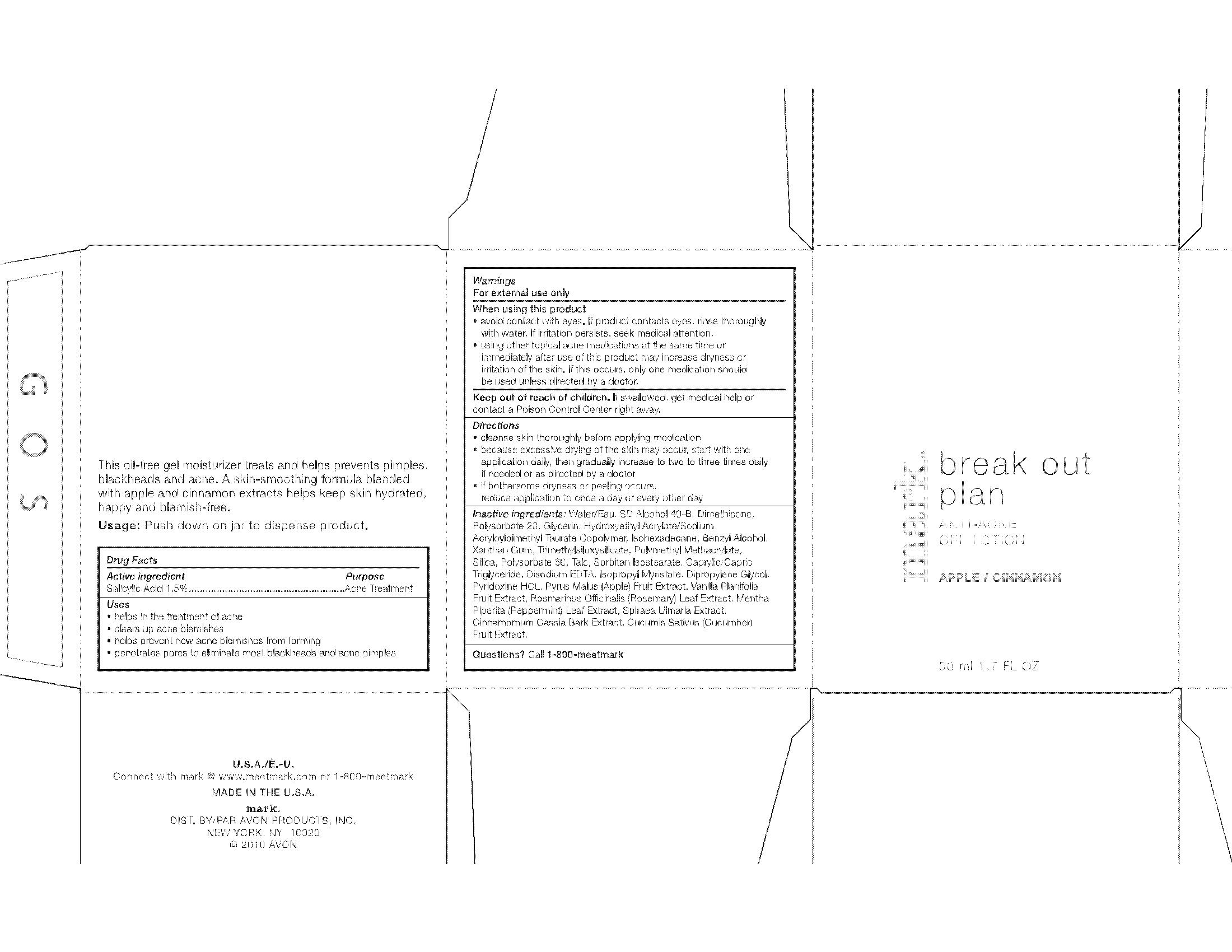 DRUG LABEL: MARK. 
NDC: 10096-0195 | Form: GEL
Manufacturer: Avon Products Inc.
Category: otc | Type: HUMAN OTC DRUG LABEL
Date: 20091229

ACTIVE INGREDIENTS: SALICYLIC ACID .75 mL/50 mL

DRUG FACTS

ACTIVE INGREDIENT

See attached 1092906 breakout plan FC.jpg

Active ingredient Purpose
Salicylic Acid 1.5%....................................Acne Treatment

Uses

- helps in the treatment of acne
- helps prevent new acne blemishes from forming
- clears up acne blemishes
- penetrates pores to eliminate most blackheads and acne pimples

Warnings
For external use only

When using this product

- avoid contact with eyes. If product contacts eyes, rinse thoroughly with water. If irritation persists, seek medical attention
- using other topical acne products at the same time or immediately after use of this product may increase dryness or irritation of the skin. If this occurs, only one product should be used unless directed by a doctor.

Keep out of reach of children. If swallowed, get medical help or contact a Poison Control Center right away.

Directions

- cleanse skin thoroughly before applying medication
- because excessive drying of the skin may occur, start with one application daily, then gradually increase to two to three times daily if needed or as directed by a doctor
- if bothersome dryness or peeling occurs, reduce application to once a day or every other day

Inactive/Non-medicinal ingredients

WATER/EAU
SD ALCOHOL 40-B
DIMETHICONE
POLYSORBATE 20
GLYCERIN
PYRUS MALUS (APPLE) FRUIT EXTRACT
VANILLA PLANIFOLIA FRUIT EXTRACT
ROSMARINUS OFFICINALIS (ROSEMARY) LEAF EXTRACT
MENTHA PIPERITA (PEPPERMINT) LEAF EXTRACT
SPIRAEA ULMARIA EXTRACT
CINNAMOMUM CASSIA BARK EXTRACT
CUCUMIS SATIVUS (CUCUMBER) FRUIT EXTRACT
HYDROXYETHYL ACRYLATE/SODIUM ACRYLOYLDIMETHYL TAURATE COPOLYMER
ISOHEXADECANE
XANTHAN GUM
TRIMETHYLSILOXYSILICATE
POLYMETHYL METHACRYLATE
SILICA
POLYSORBATE 60
TALC
SORBITAN ISOSTEARATE
CAPRYLIC/CAPRIC TRIGLYCERIDE
ISOPROPYL MYRISTATE
DIPROPYLENE GLYCOL
PYRIDOXINE HCL
DISODIUM EDTA
BENZYL ALCOHOL

Questions? Call 1-800-meetmark